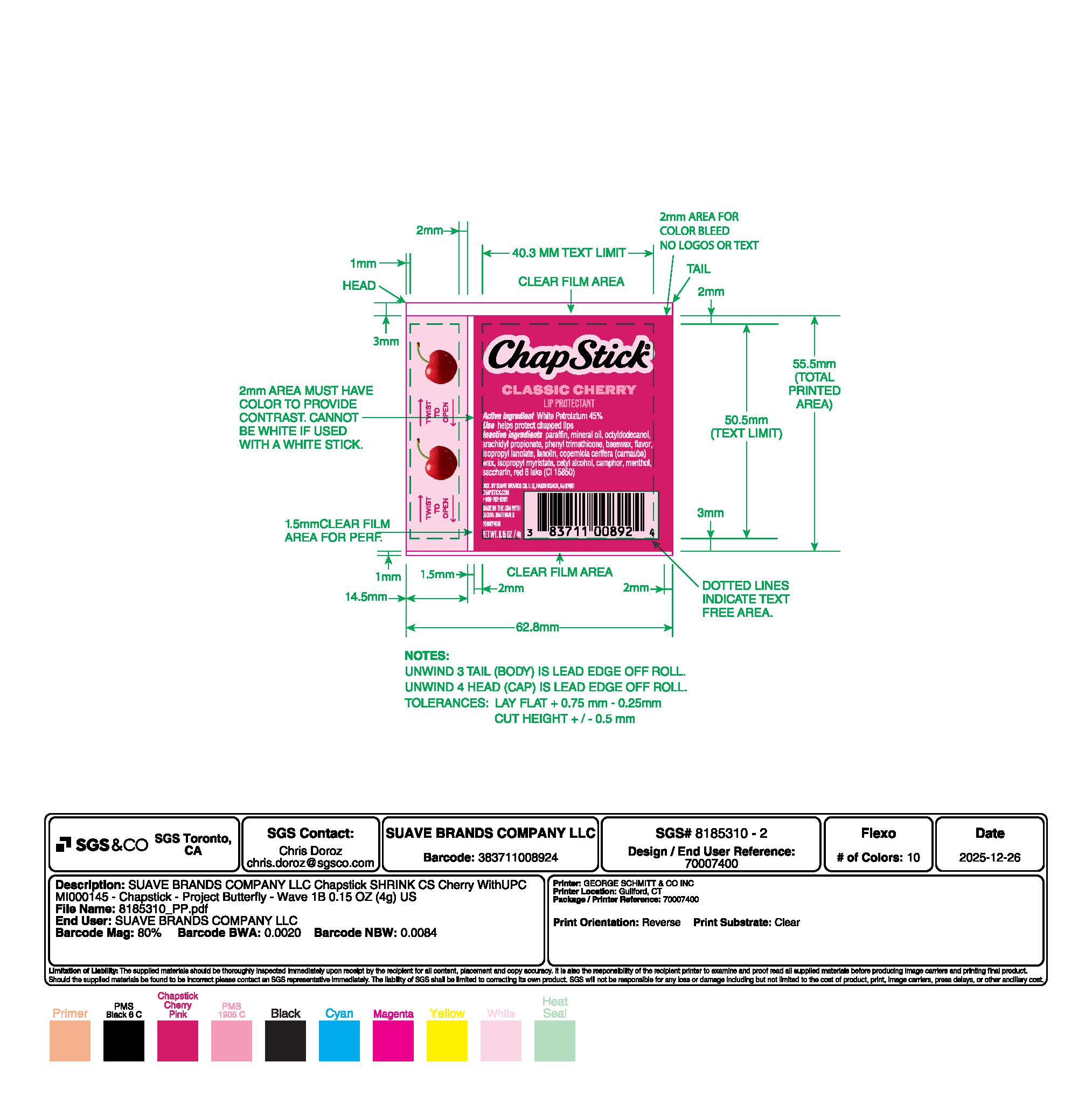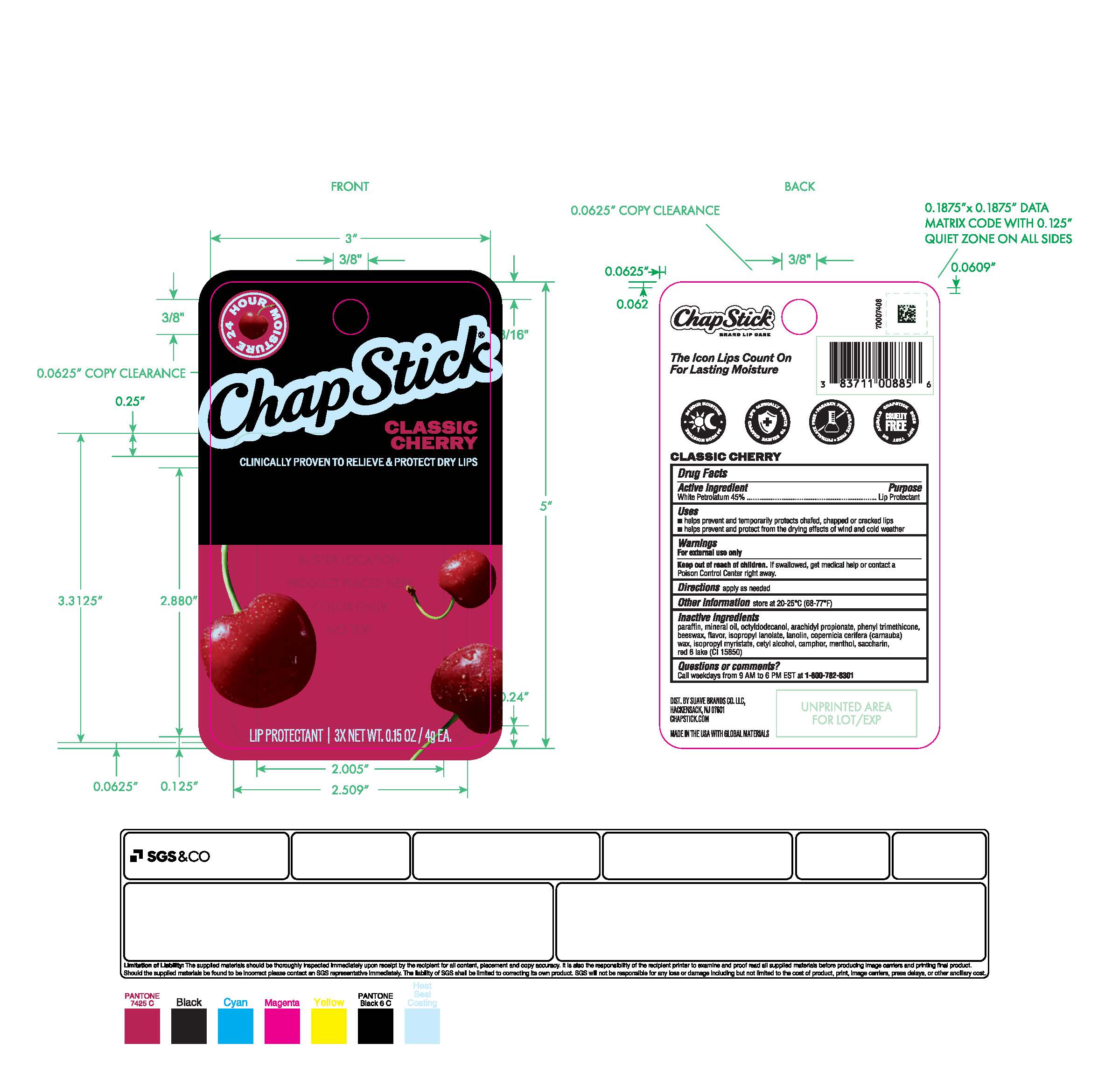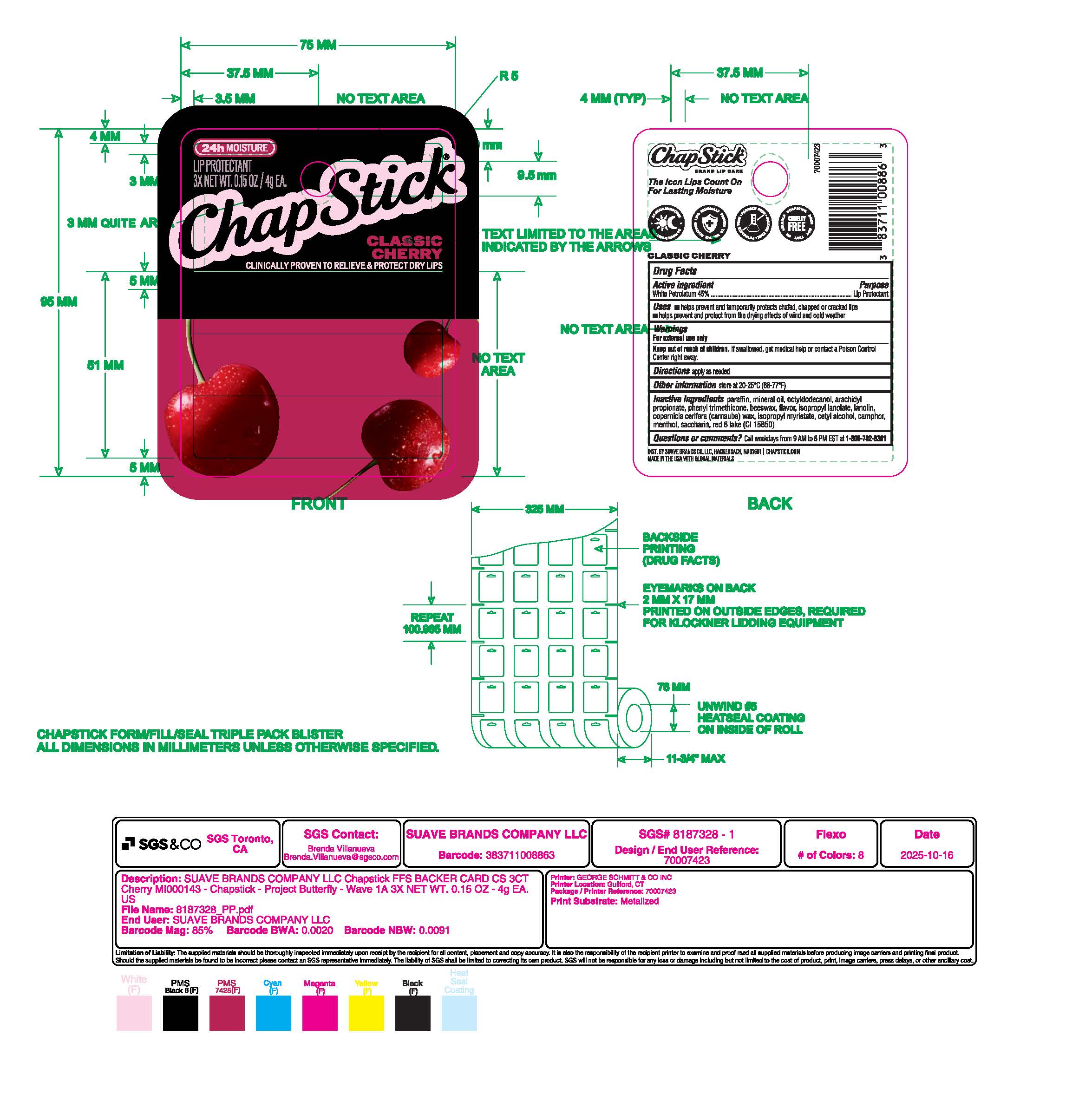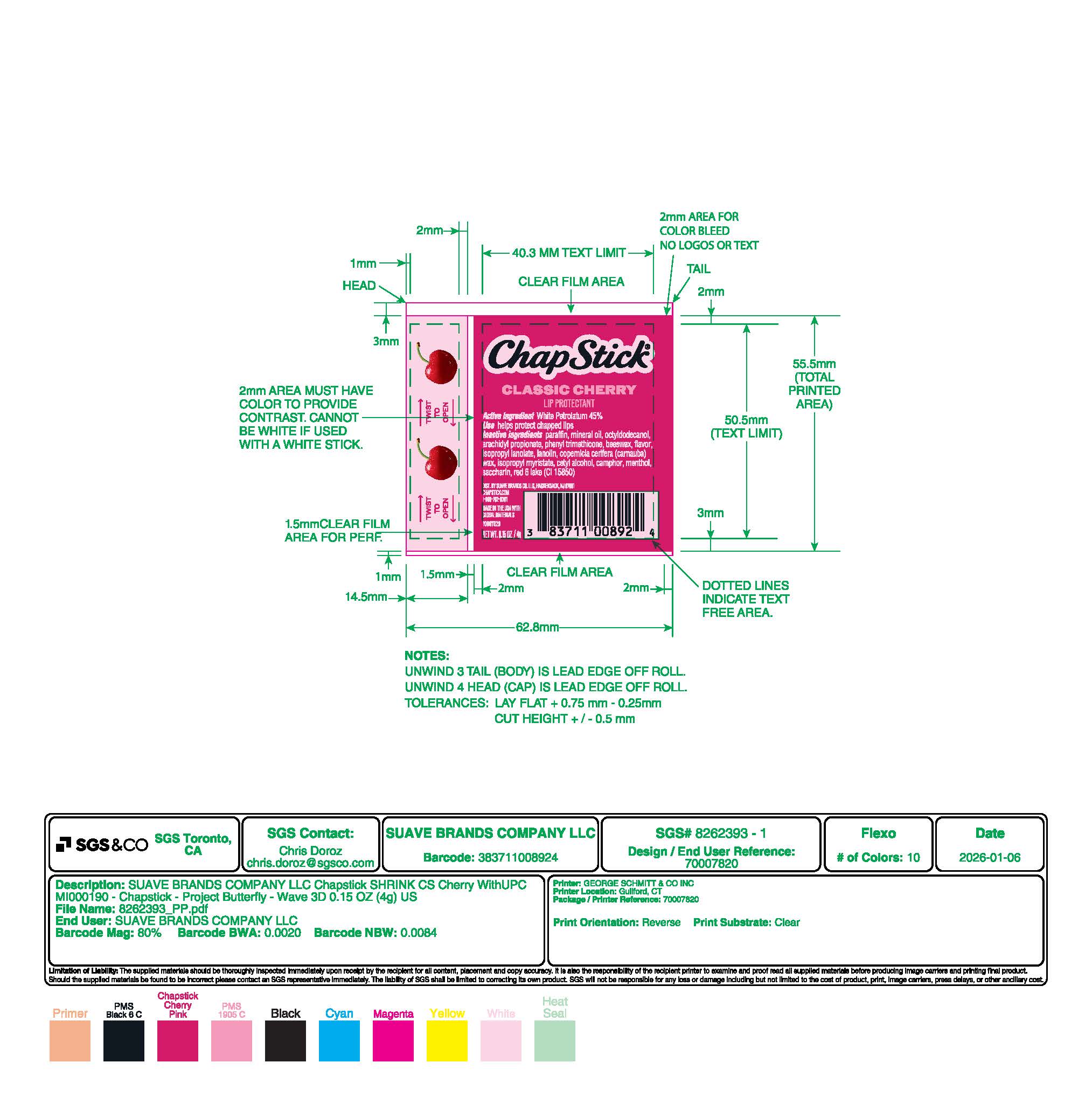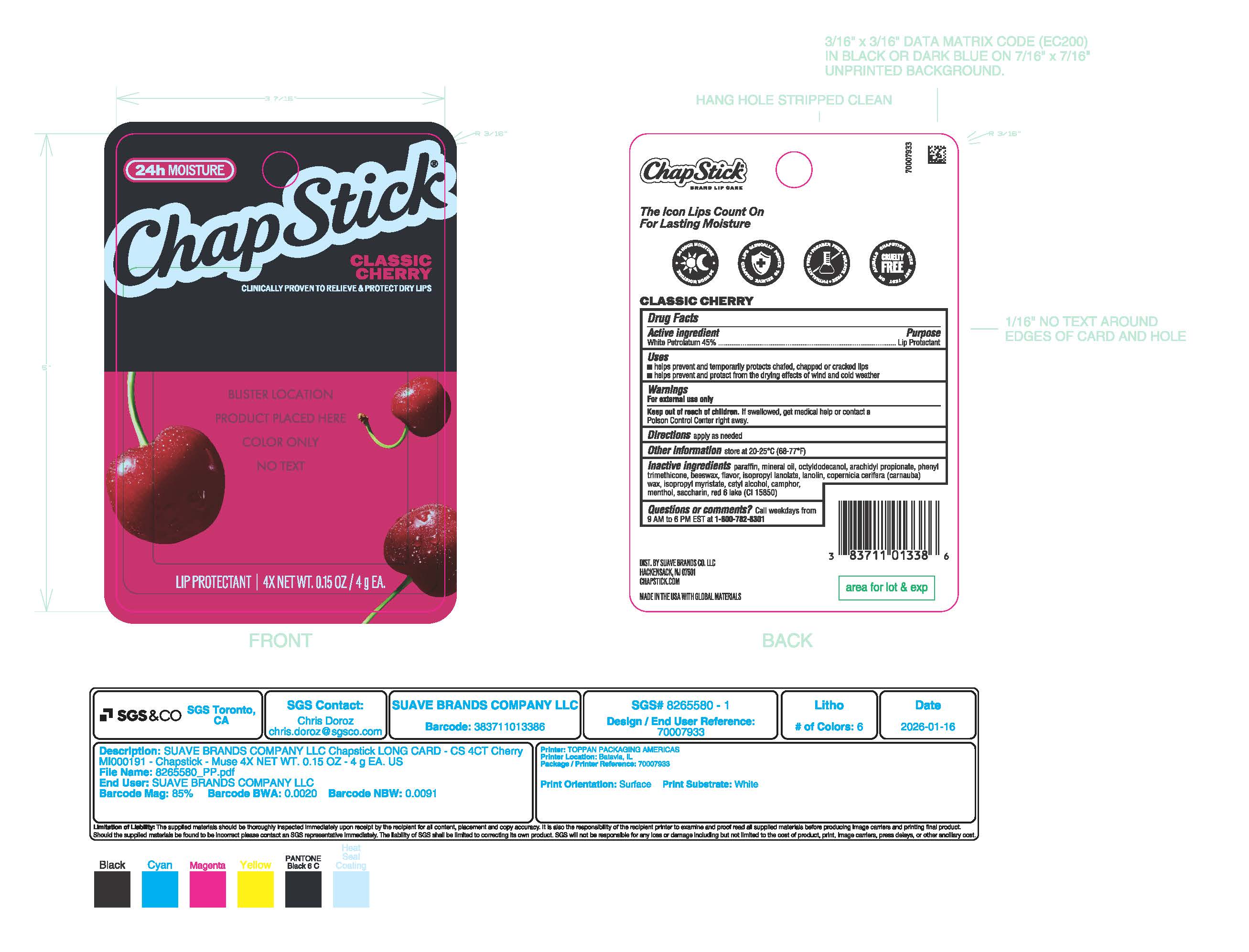 DRUG LABEL: ChapStick Classic Cherry
NDC: 83711-814 | Form: STICK
Manufacturer: Suave Brands Co., LLC
Category: otc | Type: HUMAN OTC DRUG LABEL
Date: 20260211

ACTIVE INGREDIENTS: WHITE PETROLATUM 45 g/100 g
INACTIVE INGREDIENTS: MINERAL OIL; MENTHOL; ISOPROPYL LAURATE; CETYL ALCOHOL; PARAFFIN; ARACHIDYL PROPIONATE; CAMPHOR (SYNTHETIC); SACCHARIN; ISOPROPYL MYRISTATE; PHENYL TRIMETHICONE; FLAVOR SPICE MINT N&A110589; OCTYLDODECANOL; RED 6; CARNAUBA WAX; LANOLIN; BEESWAX

Uses:

- helps prevent and temporarily protects chafed, chapped, or cracked lips
- helps prevent and protect from the drying effects of wind or cold weather

WARNINGS

For external use only

Keep out of reach of children. If swallowed, get medical help or contact a Poison Control Center right away.

Active Ingredient

White Petrolatum 45%

Purpose

Lip Protectant

Directions

Apply as needed

Other Information store at 20-25*C (68-77*F)

INACTIVE INGREDIENT

arachidyl propionate, camphor, carnauba wax, cetyl alcohol, fragrance, isopropyl lanolate, isopropyl myristate, lanolin, light mineral oil, menthol, octyldodecanol, paraffin, phenyl trimethicone, red 6 lake, saccharin, white wax

Uses:

helps prevent and temporarily protects chafed, chapped, or cracked lips
helps prevent and protect from the drying effects of wind or cold weather